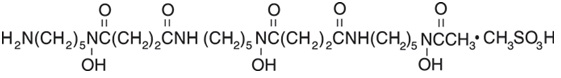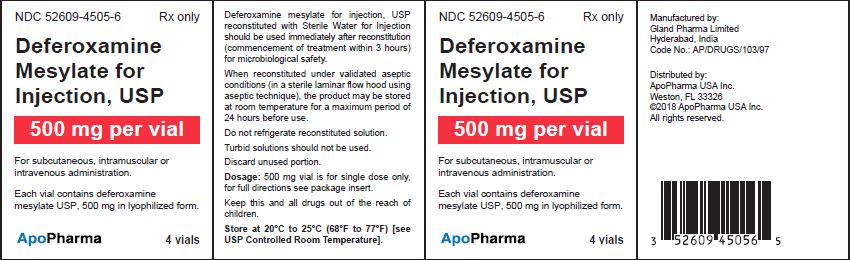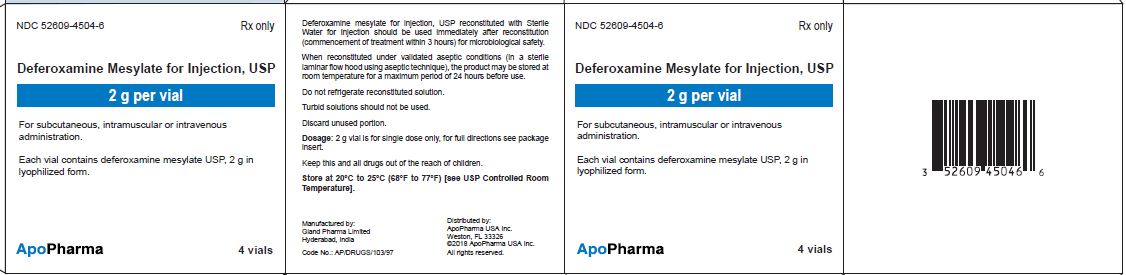 DRUG LABEL: Deferoxamine mesylate
NDC: 52609-4505 | Form: INJECTION, POWDER, LYOPHILIZED, FOR SOLUTION
Manufacturer: ApoPharma USA, Inc.
Category: prescription | Type: HUMAN PRESCRIPTION DRUG LABEL
Date: 20180323

ACTIVE INGREDIENTS: DEFEROXAMINE MESYLATE 500 mg/1 1

Deferoxamine Mesylate for Injection, USP
Vials
Rx only
Prescribing Information

DESCRIPTION

Deferoxamine mesylate for injection, USP, is an iron-chelating agent, available in vials for intramuscular, subcutaneous, and intravenous administration. Deferoxamine mesylate is supplied as vials containing 500 mg and 2 g of deferoxamine mesylate USP in sterile, lyophilized form. Deferoxamine mesylate is N-[5-[3-[(5-aminopentyl)hydroxycarbamoyl]propionamido]pentyl]-3-[[5-(N-hydroxyacetamido) pentyl]carbamoyl]propionohydroxamic acid monomethanesulfonate (salt), and its structural formula is

Deferoxamine mesylate USP is a white to off-white powder. It is freely soluble in water and slightly soluble in methanol. Its molecular weight is 656.79.

CLINICAL PHARMACOLOGY

Deferoxamine mesylate chelates iron by forming a stable complex that prevents the iron from entering into further chemical reactions. It readily chelates iron from ferritin and hemosiderin but not readily from transferrin; it does not combine with the iron from cytochromes and hemoglobin. Deferoxamine mesylate does not cause any demonstrable increase in the excretion of electrolytes or trace metals. Theoretically, 100 parts by weight of deferoxamine mesylate is capable of binding approximately 8.5 parts by weight of ferric iron.
Deferoxamine mesylate is metabolized principally by plasma enzymes, but the pathways have not yet been defined. The chelate is readily soluble in water and passes easily through the kidney, giving the urine a characteristic reddish color. Some is also excreted in the feces via the bile.

INDICATIONS & USAGE

Deferoxamine mesylate for injection, USP, is indicated for the treatment of acute iron intoxication and of chronic iron overload due to transfusion-dependent anemias.

Acute Iron Intoxication

Deferoxamine mesylate is an adjunct to, and not a substitute for, standard measures used in treating acute iron intoxication, which may include the following: induction of emesis with syrup of ipecac; gastric lavage; suction and maintenance of a clear airway; control of shock with intravenous fluids, blood, oxygen, and vasopressors; and correction of acidosis.

Chronic Iron Overload

Deferoxamine mesylate can promote iron excretion in patients with secondary iron overload from multiple transfusions (as may occur in the treatment of some chronic anemias, including thalassemia). Long-term therapy with deferoxamine mesylate slows accumulation of hepatic iron and retards or eliminates progression of hepatic fibrosis.

Iron mobilization with deferoxamine mesylate is relatively poor in patients under the age of 3 years with relatively little iron overload. The drug should ordinarily not be given to such patients unless significant iron mobilization (e.g., 1 mg or more of iron per day) can be demonstrated.

Deferoxamine mesylate is not indicated for the treatment of primary hemochromatosis, since phlebotomy is the method of choice for removing excess iron in this disorder.

CONTRAINDICATIONS

Known hypersensitivity to the active substance.

Deferoxamine mesylate is contraindicated in patients with severe renal disease or anuria, since the drug and the iron chelate are excreted primarily by the kidney. (See WARNINGS).

WARNINGS

Ocular and auditory disturbances have been reported when deferoxamine mesylate was administered over prolonged periods of time, at high doses, or in patients with low ferritin levels. The ocular disturbances observed have been blurring of vision; cataracts after prolonged administration in chronic iron overload; decreased visual acuity including visual loss, visual defects, scotoma; impaired peripheral, color, and night vision; optic neuritis, cataracts, corneal opacities, and retinal pigmentary abnormalities. The auditory abnormalities reported have been tinnitus and hearing loss including high frequency sensorineural hearing loss. In most cases, both ocular and auditory disturbances were reversible upon immediate cessation of treatment (see PRECAUTIONS/Information for Patients and ADVERSE REACTIONS/Special Senses).

Visual acuity tests, slit-lamp examinations, funduscopy and audiometry are recommended periodically in patients treated for prolonged periods of time. Toxicity is more likely to be reversed if symptoms or test abnormalities are detected early.

Increases in serum creatinine (possibly dose-related), acute renal failure and renal tubular disorders, associated with the administration of deferoxamine, have been reported in postmarketing experience (see ADVERSE REACTIONS). Monitor patients for changes in renal function.

High doses of deferoxamine mesylate and concomitant low ferritin levels have also been associated with growth retardation. After reduction of deferoxamine mesylate dose, growth velocity may partially resume to pretreatment rates (see PRECAUTIONS/Pediatric Use).

Adult respiratory distress syndrome, also reported in children, has been described following treatment with excessively high intravenous doses of deferoxamine mesylate in patients with acute iron intoxication or thalassemia.

PRECAUTIONS

General

Flushing of the skin, urticaria, hypotension, and shock have occurred in a few patients when deferoxamine mesylate was administered by rapid intravenous injection. THEREFORE, DEFEROXAMINE MESYLATE SHOULD BE GIVEN INTRAMUSCULARLY OR BY SLOW SUBCUTANEOUS OR INTRAVENOUS INFUSION.

Iron overload increases susceptibility of patients to Yersinia enterocolitica and Yersinia pseudotuberculosis infections. In some rare cases, treatment with deferoxamine mesylate has enhanced this susceptibility, resulting in generalized infections by providing these bacteria with a siderophore otherwise missing. In such cases, deferoxamine mesylate treatment should be discontinued until the infection is resolved.

In patients receiving deferoxamine mesylate, rare cases of mucormycosis, some with a fatal outcome, have been reported. If any of the suspected signs or symptoms occur, deferoxamine mesylate should be discontinued, mycological tests carried out and appropriate treatment instituted immediately.

In patients with severe chronic iron overload, impairment of cardiac function has been reported following concomitant treatment with deferoxamine mesylate and high doses of vitamin C (more than 500 mg daily in adults). The cardiac dysfunction was reversible when vitamin C was discontinued. The following precautions should be taken when vitamin C and deferoxamine mesylate are to be used concomitantly:

• Vitamin C supplements should not be given to patients with cardiac failure.

• Start supplemental vitamin C only after an initial month of regular treatment with

deferoxamine mesylate.

• Give vitamin C only if the patient is receiving deferoxamine mesylate regularly, ideally soon

after setting up the infusion pump.

• Do not exceed a daily vitamin C dose of 200 mg in adults, given in divided doses.

• Clinical monitoring of cardiac function is advisable during such combined therapy.

In patients with aluminum-related encephalopathy and receiving dialysis, deferoxamine mesylate may cause neurological dysfunction (seizures), possibly due to an acute increase in circulating aluminum (see ADVERSE REACTIONS). Deferoxamine mesylate may precipitate the onset of dialysis dementia. Treatment with deferoxamine mesylate in the presence of aluminum overload may result in decreased serum calcium and aggravation of hyperparathyroidism.

Drug Interactions

Vitamin C: Patients with iron overload usually become vitamin C deficient, probably because iron oxidizes the vitamin. As an adjuvant to iron chelation therapy, vitamin C in doses up to 200 mg for adults may be given in divided doses, starting after an initial month of regular treatment with deferoxamine mesylate (see PRECAUTIONS). Vitamin C increases availability of iron for chelation. In general, 50 mg daily suffices for children under 10 years old and 100 mg daily for older children. Larger doses of vitamin C fail to produce any additional increase in excretion of iron complex.

Prochlorperazine: Concurrent treatment with deferoxamine mesylate and prochlorperazine, a phenothiazine derivative, may lead to temporary impairment of consciousness.

Gallium-67: Imaging results may be distorted because of the rapid urinary excretion of deferoxamine mesylate-bound gallium-67. Discontinuation of deferoxamine mesylate 48 hours prior to scintigraphy is advisable.

Information for Patients

Patients experiencing dizziness or other nervous system disturbances, or impairment of vision or hearing, should refrain from driving or operating potentially hazardous machines (see ADVERSE REACTIONS).

Patients should be informed that occasionally their urine may show a reddish discoloration.

Carcinogenesis, Mutagenesis, Impairment of Fertility

Long-term carcinogenicity studies in animals have not been performed with deferoxamine mesylate.

Cytotoxicity may occur, since deferoxamine mesylate has been shown to inhibit DNA synthesis in vitro.

Pregnancy Category C

Delayed ossification in mice and skeletal anomalies in rabbits were observed after deferoxamine mesylate was administered in daily doses up to 4.5 times the maximum daily human dose. No adverse effects were observed in similar studies in rats.

There are no adequate and well-controlled studies in pregnant women. Deferoxamine mesylate should be used during pregnancy only if the potential benefit justifies the potential risk to the fetus.

Nursing Mothers

It is not known whether this drug is excreted in human milk. Because many drugs are excreted in

human milk, caution should be exercised when deferoxamine mesylate is administered to a nursing woman.

Pediatric Use

Pediatric patients receiving deferoxamine mesylate should be monitored for body weight and growth every 3 months.

Safety and effectiveness in pediatric patients under the age of 3 years have not been established (see INDICATIONS AND USAGE, WARNINGS, PRECAUTIONS/Drug Interactions/Vitamin C, and ADVERSE REACTIONS).

Geriatric Use

Clinical Studies of deferoxamine mesylate did not include sufficient numbers of subjects aged 65 years and over to determine whether they respond differently from the younger subjects. Postmarketing reports suggest a possible trend for an increased risk of eye disorders in the geriatric population, specifically the occurrence of color blindness, maculopathy, and scotoma. However, it is unclear if these eye disorders were dose related. Although the number of reports was very small, certain elderly patients may be predisposed to eye disorders when taking deferoxamine mesylate. Postmarketing reports also suggest that there may be an increased risk of deafness and hearing loss in the geriatric population. (see ADVERSE REACTIONS). In general, dose selection for an elderly patient should be cautious, usually starting at the low end of the dosing range, reflecting the greater frequency of decreased hepatic, renal, or cardiac function, and of concomitant disease or other drug therapy.

Hepatic Impairment

No studies have been performed in patients with hepatic impairment.

ADVERSE REACTIONS

The following adverse reactions have been observed, but there are not enough data to support an estimate of their frequency.

At the Injection Site: Localized irritation, pain, burning, swelling, induration, infiltration, pruritus, erythema, wheal formation, eschar, crust, vesicles, local edema. Injection site reactions may be associated with systemic allergic reactions (see Body as a Whole, below).

Hypersensitivity Reactions and Systemic Allergic Reactions: Generalized rash, urticaria, anaphylactic reaction with or without shock, angioedema.

Body as a Whole: Local injection site reactions may be accompanied by systemic reactions like arthralgia, fever, headache, myalgia, nausea, vomiting, abdominal pain, or asthma.

Infections with Yersinia and Mucormycosis have been reported in association with deferoxamine mesylate use (see PRECAUTIONS).

Cardiovascular: Tachycardia, hypotension, shock.

Digestive: Abdominal discomfort, diarrhea, nausea, vomiting.

Hematologic: Blood dyscrasia (thrombocytopenia, leucopenia).

Hepatic: Increased transaminases, hepatic dysfunction.

Musculoskeletal: Muscle spasms. Growth retardation and bone changes (e.g., metaphyseal dysplasia) are common in chelated patients given doses above 60 mg/kg, especially those who begin iron chelation in the first three years of life. If doses are kept to 40 mg/kg or below, the risk may be reduced (see WARNINGS, PRECAUTIONS/Pediatric Use).

Nervous System: Neurological disturbances including dizziness, peripheral sensory, motor, or mixed neuropathy, paresthesias, seizures; exacerbation or precipitation of aluminum-related dialysis encephalopathy (see PRECAUTIONS/Information for Patients).

Special Senses: High-frequency sensorineural hearing loss and/or tinnitus are uncommon if dosage guidelines are not exceeded and if dose is reduced when ferritin levels decline. Visual disturbances are rare if dosage guidelines are not exceeded. These may include decreased acuity, blurred vision, loss of vision, dyschromatopsia, night blindness, visual field defects, scotoma, retinopathy (pigmentary degeneration), optic neuritis, and cataracts (see WARNINGS).

Respiratory: Acute respiratory distress syndrome (with dyspnea, cyanosis, and/or interstitial infiltrates) (see WARNINGS).

Skin: Very rare generalized rash.

Urogenital: Dysuria, acute renal failure, increased serum creatinine and renal tubular disorders (see CONTRAINDICATIONS and WARNINGS).

Postmarketing Reports

There are postmarketing reports of deferoxamine-associated renal dysfunction, including renal failure. Monitor patients for changes in renal function (e.g., increased serum creatinine).

OVERDOSAGE

Acute Toxicity

Intravenous LD50s (mg/kg): mice, 287; rats, 329.

Signs and Symptoms

Inadvertent administration of an overdose or inadvertent intravenous bolus administration/rapid intravenous infusion may be associated with hypotension, tachycardia and gastrointestinal disturbances; acute but transient loss of vision, aphasia, agitation, headache, nausea, pallor, CNS depression including coma, bradycardia and acute renal failure have been reported.

Acute respiratory distress syndrome has been reported following treatment with excessively high intravenous doses of deferoxamine mesylate in patients with acute iron intoxication and in patients with thalassemia.

Treatment

There is no specific antidote. Deferoxamine mesylate should be discontinued and appropriate symptomatic measures undertaken.

Deferoxamine mesylate is readily dialyzable.

DOSAGE & ADMINISTRATION

Acute Iron Intoxication

Intramuscular Administration

This route is preferred and should be used for ALL PATIENTS NOT IN SHOCK.

A dose of 1000 mg should be administered initially. This may be followed by 500 mg every 4 hours for two doses. Depending upon the clinical response, subsequent doses of 500 mg may be administered every 4-12 hours. The total amount administered should not exceed 6000 mg in 24 hours. For reconstitution instructions for intramuscular administration see Table 1.

Intravenous Administration

THIS ROUTE SHOULD BE USED ONLY FOR PATIENTS IN A STATE OF CARDIOVASCULAR COLLAPSE AND THEN ONLY BY SLOW INFUSION. THE RATE OF INFUSION SHOULD NOT EXCEED 15 MG/KG/HR FOR THE FIRST 1000 MG ADMINISTERED. SUBSEQUENT IV DOSING, IF NEEDED, MUST BE AT A SLOWER RATE, NOT TO EXCEED 125 MG/HR.

For reconstitution instructions for intravenous administration see Table 2. The reconstituted solution is added to physiologic saline, (e.g., 0.9% sodium chloride, 0.45% sodium chloride), glucose in water, or Ringer’s lactate solution.

An initial dose of 1000 mg should be administered at a rate NOT TO EXCEED 15 mg/kg/hr. This may be followed by 500 mg over 4 hours for two doses. Depending upon the clinical response, subsequent doses of 500 mg may be administered over 4-12 hours. The total amount administered should not exceed 6000 mg in 24 hours.

As soon as the clinical condition of the patient permits, intravenous administration should be discontinued and the drug should be administered intramuscularly.

CHRONIC IRON OVERLOAD

Subcutaneous Administration

A daily dose of 1000-2000 mg (20-40 mg/kg/day) should be administered over 8-24 hours, utilizing a small portable pump capable of providing continuous mini-infusion. The duration of infusion must be individualized. In some patients, as much iron will be excreted after a short infusion of 8-12 hours as with the same dose given over 24 hours. For reconstitution instructions for subcutaneous administration see Table 3.

Intravenous Administration

The standard recommended method of deferoxamine mesylate administration is via slow subcutaneous infusion over 8 – 12 hours. In patients with intravenous access, the daily dose of deferoxamine mesylate can be administered intravenously. The standard dose is 20 – 40 mg/kg/day for children and 40 – 50 mg/kg/day over 8 – 12 hours in adults for 5 – 7 days per week. In children, average doses should not exceed 40 mg/kg/day until growth has ceased. In adults, average doses should not exceed 60 mg/kg/day. The intravenous infusion rate should not exceed 15 mg/kg/hour. For reconstitution instructions for intravenous administration see Table 2.

In patients who are poorly compliant, deferoxamine mesylate may be administered prior to or following same day blood transfusion (for example 1 gram over 4 hours on the day of transfusion); however, the contribution of this mode of administration to iron balance is limited. Deferoxamine mesylate should not be administered concurrently with the blood transfusion as this can lead to errors in interpreting side effects such as rash, anaphylaxis and hypotension.

Intramuscular Administration

A daily dose of 500-1000 mg may be administered intramuscularly. The total daily dose should not exceed 1000 mg. For reconstitution instructions for intramuscular administration see Table 1.

Reconstitution and Preparation

Table 1: Preparation for Intramuscular Administration

RECONSTITUTE DEFEROXAMINE MESYLATE WITH STERILE WATER FOR INJECTION
Vial Size | Amount of Sterile Water for Injection Required for Reconstitution | Total Drug Content after Reconstitution | Final Concentration per mL after Reconstitution
500 mg | 2 mL | 500 mg/2.35 mL | 213 mg/mL
2 grams | 8 mL | 2 grams/9.4 mL | 213 mg/mL

Table 2: Preparation for Intravenous Administrations

RECONSTITUTE DEFEROXAMINE MESYLATE WITH STERILE WATER FOR INJECTION
Vial Size | Amount of Sterile Water for Injection Required for Reconstitution | Total Drug Content after Reconstitution | Final Concentration per mL after Reconstitution
500 mg | 5 mL | 500 mg/5.3 mL | 95 mg/mL
2 grams | 20 mL | 2 grams/21.1 mL | 95 mg/mL

Table 3: Preparation for Subcutaneous Administration

RECONSTITUTE DEFEROXAMINE MESYLATE WITH STERILE WATER FOR INJECTION
Vial Size | Amount of Sterile Water for Injection Required for Reconstitution | Total Drug Content after Reconstitution | Final Concentration per mL after Reconstitution
500 mg | 5 mL | 500 mg/5.3 mL | 95 mg/mL
2 grams | 20 mL | 2 grams/21.1 mL | 95 mg/mL

The reconstituted deferoxamine mesylate solution is an isotonic, clear and colorless to slightly- yellowish solution. The drug should be completely dissolved before the solution is withdrawn. Deferoxamine mesylate for injection reconstituted with Sterile Water for Injection IS FOR SINGLE DOSE ONLY. Discard unused portion.

The product should be used immediately after reconstitution (commencement of treatment within 3 hours) for microbiological safety. When reconstitution is carried out under validated aseptic conditions (in a sterile laminar flow hood using aseptic technique), the product may be stored at room temperature for a maximum period of 24 hours before use. Do not refrigerate reconstituted solution. Reconstituting deferoxamine mesylate for injection in solvents or under conditions other than indicated may result in precipitation. Turbid solutions should not be used.

HOW SUPPLIED

Vials - each containing 500 mg of sterile, lyophilized deferoxamine mesylate

Cartons of 4 vials……………………………………………NDC 52609-4505-6

Vials - each containing 2 g of sterile, lyophilized deferoxamine mesylate

Cartons of 4 vials……………………………………………NDC 52609-4504-6
Each vial is for single use only.
Discard unused portion.
Store at 20° to 25°C (68° to 77°F) [See USP Controlled Room Temperature].

PACKAGE LABEL.PRINCIPAL DISPLAY PANEL

Package Label – 500 mg per vial

NDC 52609-4505-6

Rx only

Deferoxamine mesylate for Injection, USP

500 mg per vial

For subcutaneous, intramuscular or intravenous administration.

Each vial contains deferoxamine mesylate USP, 500 mg in lyophilized form.

4 vials

Package Label – 2 g per vial

NDC 52609-4504-6

Rx only

Deferoxamine mesylate for Injection, USP

2 g per vial

For subcutaneous, intramuscular or intravenous administration.

Each vial contains deferoxamine mesylate USP, 2 g in lyophilized form.

4 vials